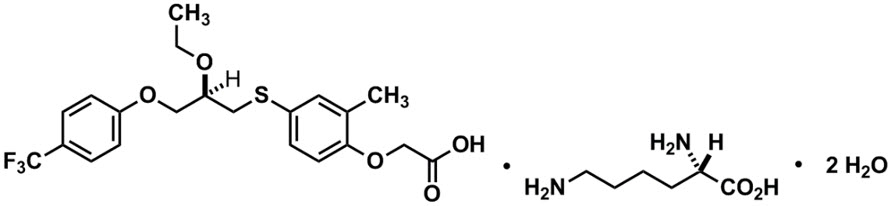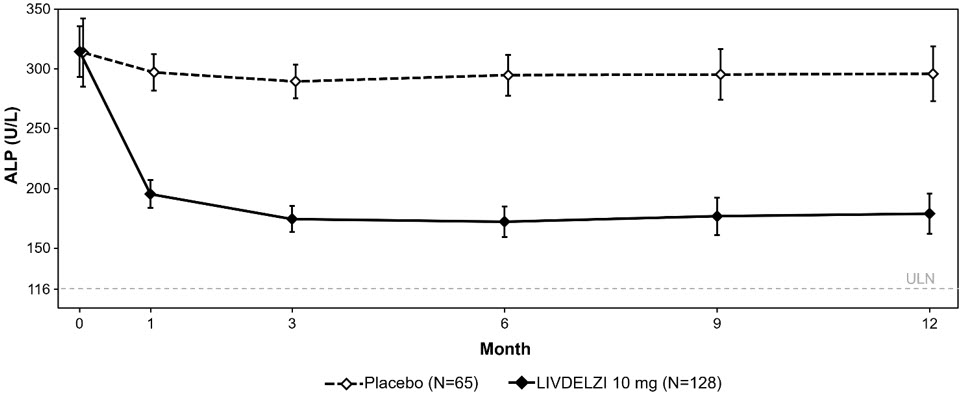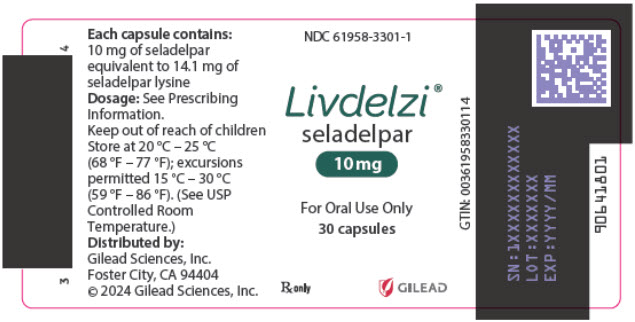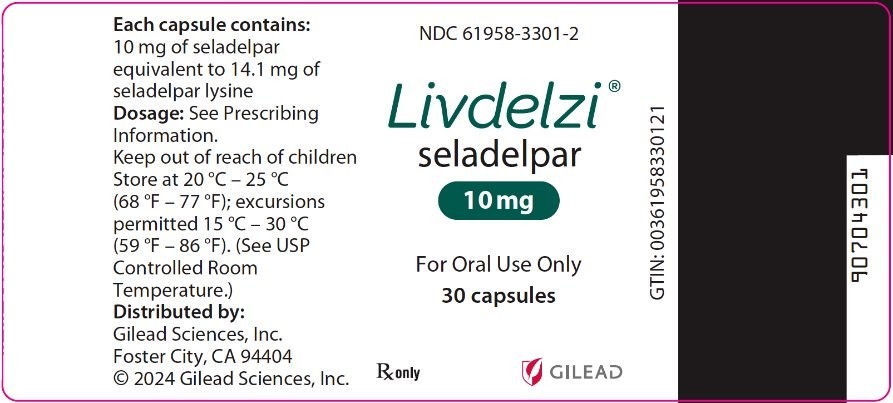 DRUG LABEL: Livdelzi
NDC: 61958-3301 | Form: CAPSULE
Manufacturer: Gilead Sciences, Inc
Category: prescription | Type: HUMAN PRESCRIPTION DRUG LABEL
Date: 20260203

ACTIVE INGREDIENTS: SELADELPAR LYSINE 10 mg/1 1
INACTIVE INGREDIENTS: MANNITOL; MICROCRYSTALLINE CELLULOSE 302; MICROCRYSTALLINE CELLULOSE 101; CROSCARMELLOSE SODIUM; MAGNESIUM STEARATE; SILICON DIOXIDE; Butylated hydroxytoluene

HIGHLIGHTS OF PRESCRIBING INFORMATION

These highlights do not include all the information needed to use LIVDELZI safely and effectively. See full prescribing information for LIVDELZI.
LIVDELZI® (seladelpar) capsules, for oral use
Initial U.S. Approval: 2024

1 INDICATIONS AND USAGE

LIVDELZI is a peroxisome proliferator-activated receptor (PPAR)-delta agonist indicated for the treatment of primary biliary cholangitis (PBC) in combination with ursodeoxycholic acid (UDCA) in adults who have an inadequate response to UDCA, or as monotherapy in patients unable to tolerate UDCA.

This indication is approved under accelerated approval based on a reduction of alkaline phosphatase (ALP). Improvement in survival or prevention of liver decompensation events have not been demonstrated. Continued approval for this indication may be contingent upon verification and description of clinical benefit in confirmatory trial(s). (1)

Limitations of Use

Use of LIVDELZI is not recommended in patients who have or develop decompensated cirrhosis (e.g., ascites, variceal bleeding, hepatic encephalopathy). (8.7)

2 DOSAGE AND ADMINISTRATION

The recommended dosage of LIVDELZI is 10 mg orally once daily. Administer LIVDELZI with or without food. (2.1)

3 DOSAGE FORMS AND STRENGTHS

Capsules: 10 mg (3)

4 CONTRAINDICATIONS

None.

5 WARNINGS AND PRECAUTIONS

- Fractures: Consider the risk of fracture in patients treated with LIVDELZI. Monitor bone health according to current standards of care. (5.1)
- Liver Test Abnormalities: Obtain baseline clinical and laboratory liver assessments prior to starting LIVDELZI and monitor during treatment. Interrupt or discontinue LIVDELZI if the liver tests worsen. (5.2)
- Biliary Obstruction: Avoid use in patients with complete biliary obstruction. If biliary obstruction is suspected, interrupt LIVDELZI and treat as clinically indicated. (5.3)

6 ADVERSE REACTIONS

Most common adverse reactions (reported in ≥5% and higher compared to placebo) are headache, abdominal pain, nausea, abdominal distension, and dizziness. (6.1)

To report SUSPECTED ADVERSE REACTIONS, contact Gilead Sciences, Inc. at 1-800-GILEAD-5 or FDA at 1-800-FDA-1088 or www.fda.gov/medwatch.

7 DRUG INTERACTIONS

- Probenecid: Avoid concomitant use. (7.1)
- Strong CYP2C9 Inhibitors: Monitor for adverse effects. (7.1)
- Dual Moderate CYP2C9 and Moderate to Strong CYP3A4 Inhibitors: Monitor for adverse effects. (7.1)
- CYP2C9 Poor Metabolizers using Moderate to Strong CYP3A4 Inhibitors: Monitor for adverse effects. (7.1)
- Dual or Multiple Clinical Inhibitors of Drug Transporters OATP1B1, OATP1B3, and BCRP: Monitor for adverse effects. (7.1)
- Rifampin: Monitor biochemical response (e.g., ALP and bilirubin) when patients initiate rifampin. (7.1)
- Bile Acid Sequestrants: Administer at least 4 hours before or 4 hours after taking a bile acid sequestrant, or at as great an interval as possible. (7.1)

8 USE IN SPECIFIC POPULATIONS

Hepatic Impairment: Monitor patients with cirrhosis for evidence of decompensation. Consider discontinuation if patient progresses to moderate or severe hepatic impairment (Child-Pugh B or C). (8.7)

FULL PRESCRIBING INFORMATION

1 INDICATIONS AND USAGE

LIVDELZI is indicated for the treatment of primary biliary cholangitis (PBC) in combination with ursodeoxycholic acid (UDCA) in adults who have had an inadequate response to UDCA, or as monotherapy in patients unable to tolerate UDCA.

This indication is approved under accelerated approval based on a reduction of alkaline phosphatase (ALP) [see Clinical Studies (14)]. Improvement in survival or prevention of liver decompensation events have not been demonstrated. Continued approval for this indication may be contingent upon verification and description of clinical benefit in confirmatory trial(s).

Limitations of Use

Use of LIVDELZI is not recommended in patients who have or develop decompensated cirrhosis (e.g., ascites, variceal bleeding, hepatic encephalopathy) [see Use in Specific Populations (8.7)].

2 DOSAGE AND ADMINISTRATION

2.1 Recommended Dosage and Administration

The recommended dosage of LIVDELZI is 10 mg orally once daily. Administer LIVDELZI with or without food [see Clinical Pharmacology (12.3)].

2.2 Administration Modification for Bile Acid Sequestrants

Administer LIVDELZI at least 4 hours before or 4 hours after taking bile acid sequestrants, or at as great an interval as possible [see Drug Interactions (7.1)].

3 DOSAGE FORMS AND STRENGTHS

Capsules: 10 mg, opaque, hard gelatin capsules, size 1, with light gray opaque body and a dark blue opaque cap, printed with "CBAY" on the cap and "10" on the body.

4 CONTRAINDICATIONS

None.

5 WARNINGS AND PRECAUTIONS

5.1 Fractures

Fractures occurred in 4% of LIVDELZI-treated patients compared to no placebo-treated patients [see Adverse Reactions (6.1)].

Consider the risk of fracture in the care of patients treated with LIVDELZI and monitor bone health according to current standards of care.

5.2 Liver Test Abnormalities

LIVDELZI has been associated with dose-related increases in serum transaminase (aspartate aminotransferase [AST] and alanine aminotransferase [ALT]) levels greater than 3-times upper limit of normal (ULN) in PBC patients receiving 50 mg once daily (5-times higher than the recommended dosage) and 200 mg (20-times higher than the recommended dosage) once daily. Transaminase levels returned to pretreatment levels upon LIVDELZI discontinuation. LIVDELZI 10 mg once daily did not show a similar pattern for increases in transaminase levels [see Overdosage (10)].

Obtain baseline clinical and laboratory assessments at treatment initiation with LIVDELZI and monitor thereafter according to routine patient management. Interrupt LIVDELZI treatment if the liver tests (ALT, AST, total bilirubin [TB], and/or alkaline phosphatase [ALP]) worsen, or the patient develops signs and symptoms consistent with clinical hepatitis (e.g., jaundice, right upper quadrant pain, eosinophilia). Consider permanent discontinuation if liver tests worsen after restarting LIVDELZI.

5.3 Biliary Obstruction

Avoid use of LIVDELZI in patients with complete biliary obstruction. If biliary obstruction is suspected, interrupt LIVDELZI and treat as clinically indicated.

6 ADVERSE REACTIONS

The following clinically significant adverse reactions are described elsewhere in labeling:

- Fractures [see Warnings and Precautions (5.1)]
- Liver Test Abnormalities [see Warnings and Precautions (5.2)]

6.1 Clinical Trial Experience

Because clinical trials are conducted under widely varying conditions, adverse reaction rates observed in the clinical trials of a drug cannot be directly compared to rates in the clinical trials of another drug and may not reflect the rates observed in practice.

In Trial 1, 193 patients were randomized to receive either LIVDELZI 10 mg (N=128) or placebo (N=65) once daily for 12 months [see Clinical Studies (14)]. LIVDELZI or placebo was administered in combination with UDCA in 94% of patients and as monotherapy in 6% of patients who were unable to tolerate UDCA.

Common Adverse Reactions

Table 1 presents common adverse reactions that occurred in Trial 1.

Table 1: Common Adverse Reactions Occurring Through Week 52 in Adult Patients with PBC (Trial 1) [Included 12 patients (6%) who were intolerant to UDCA and initiated treatment as monotherapy: 8 patients (6%) in the LIVDELZI 10 mg arm and 4 patients (6%) in the placebo arm.]
Adverse Reaction [Occurring in greater than or equal to 5% of patients in the LIVDELZI treatment arm and at an incidence greater than or equal to 1% higher than in the placebo arm.] | LIVDELZI 10 mg Once Daily (N=128) % (n) | PLACEBO (N=65) % (n)
Headache | 8% (10) | 3% (2)
Abdominal pain [The gastrointestinal adverse reactions were mild to moderate without the need for discontinuation of LIVDELZI.] | 7% (9) | 2% (1)
Nausea | 6% (8) | 5% (3)
Abdominal distension | 6% (8) | 3% (2)
Dizziness | 5% (6) | 2% (1)

Fractures

In Trial 1, fractures occurred in 4% (n=5) of LIVDELZI-treated patients compared to no placebo-treated patients. Baseline bone mineral density was not obtained. The median time to fracture after receiving LIVDELZI was 295 days (range: 89–349).

Less Common Adverse Reactions

Additional adverse reactions that occurred more frequently in the LIVDELZI-treated patients compared to placebo, but in less than 5% of patients, included dyspepsia, rash, alopecia, anemia, and cough.

Laboratory Abnormalities

Estimated Glomerular Filtration Rate

In Trial 1, LIVDELZI-treated patients developed decreased estimated glomerular filtration rate (eGFR) (serum creatinine elevations) more frequently compared to placebo-treated patients. Ten percent (n=12) of LIVDELZI-treated patients had a decline in eGFR of at least 25%, compared to 2% (n=1) of placebo-treated patients. None of the patients experienced an eGFR decline of 50% or more. The decline in eGFR stabilized or returned towards baseline with ongoing LIVDELZI treatment. None of the patients required discontinuation of LIVDELZI and there were no clinical findings associated with the observed changes in eGFR.

7 DRUG INTERACTIONS

7.1 Effect of Other Drugs on LIVDELZI

Table 2 includes clinically significant drug interactions affecting LIVDELZI.

Table 2: Clinically Significant Interactions Affecting LIVDELZI
Concomitant Drug or Class | Potential Effect on Seladelpar Exposure [↑ = Increase, ↓ = Decrease.] | Clinical Intervention
Probenecid | ↑ seladelpar | Avoid concomitant administration of LIVDELZI with probenecid.
Strong CYP2C9 Inhibitors | ↑ seladelpar | Monitor patients for adverse effects during concomitant use of LIVDELZI with strong CYP2C9 inhibitors.
Dual Moderate CYP2C9 and Moderate or Strong CYP3A4 Inhibitors (e.g., fluconazole) | ↑ seladelpar | Monitor patients for adverse effects during concomitant use of LIVDELZI with drugs that are dual moderate CYP2C9 and moderate or strong CYP3A4 inhibitors.
CYP2C9 Poor Metabolizers Using Moderate or Strong CYP3A4 Inhibitors | ↑ seladelpar | Monitor patients who are CYP2C9 poor metabolizers for adverse effects during concomitant use of LIVDELZI with moderate or strong CYP3A4 inhibitor.
Dual or Multiple Clinical Inhibitors of Drug Transporters OATP1B1, OATP1B3, and BCRP (e.g, cyclosporine) | ↑ seladelpar | Monitor patients for adverse effects during concomitant use of LIVDELZI with dual or multiple clinical inhibitors of drug transporters OATP1B1, OATP1B3, and BCRP.
Rifampin | ↓ seladelpar | Concomitant use of LIVDELZI with rifampin, an inducer of metabolizing enzymes, may result in delayed or suboptimal LIVDELZI biochemical response. Monitor the biochemical response (e.g., ALP and bilirubin) when patients initiate rifampin during LIVDELZI treatment.
Bile Acid Sequestrants | ↓ seladelpar | Bile acid sequestrants may interfere with the action of LIVDELZI by reducing its absorption and systemic exposure, which may reduce LIVDELZI efficacy. Administer LIVDELZI at least 4 hours before or 4 hours after taking a bile acid sequestrant, or at as great an interval as possible [see Dosage and Administration (2.2)].

8 USE IN SPECIFIC POPULATIONS

8.1 Pregnancy

Risk Summary

There are insufficient data from human pregnancies exposed to LIVDELZI to allow an assessment of a drug-associated risk of major birth defects, miscarriage, or other adverse maternal or fetal outcomes. In animal reproduction studies, no malformations or effects on embryo-fetal survival occurred in pregnant rats or rabbits after seladelpar treatment at exposures of up to 176-times and 49-times the recommended dose based on AUC (area under the plasma concentration-time curve), respectively. Reduction of fetal growth associated with maternal toxicity occurred in pregnant rabbits at 49-times the recommended dose based on AUC, but not at 3-times the recommended dose. In a pre- and postnatal development study in rats with maternal dosing of seladelpar during organogenesis through lactation, postnatal growth and pre-weaning survival of offspring was reduced at 115-times the recommended dose based on AUC, but not at the lower exposure of 16-times the recommended dose (see Data).

The background risks of major birth defects and miscarriage for the indicated population are unknown. All pregnancies have a background risk of birth defect, loss, or other adverse outcomes. In the U.S. general population, the estimated background risk of major birth defects and miscarriage in clinically recognized pregnancies is 2% to 4% and 15% to 20%, respectively.

Report pregnancies to Gilead Sciences, Inc. at 1-800-445-3235.

Data

Animal Data

No effects on embryo-fetal development were observed in pregnant rats treated orally with up to 100 mg/kg/day seladelpar (176-times the recommended dose based on AUC) during the period of organogenesis.

Oral administration of 40 mg/kg/day seladelpar in pregnant rabbits (49-times the recommended dose based on AUC) during organogenesis resulted in reduced fetal body weight, which was likely due to maternal toxicity (i.e., decreases in food consumption, body weight, and gravid uterine weight) and distended stomach. No treatment-related fetal malformations or effects on embryo-fetal survival occurred in rabbits at 49-times the recommended dose. No adverse effects on embryo-fetal development were observed at 10 mg/kg/day (3-times the recommended dose based on AUC).

A pre- and postnatal development study was performed using oral administration of seladelpar at doses of 0 (vehicle), 5, 20, or 100 mg/kg/day in pregnant rats during organogenesis through lactation. Treatment with 5 mg/kg/day or higher (4-times the recommended dose based on AUC) resulted in a dose-dependent reduction in pup body weight during the pre-weaning period. The weight reduction in offspring was associated with delays in developmental milestones (i.e., eye opening and pinna unfolding at 5 mg/kg/day and higher; hair growth and sexual maturity at 100 mg/kg/day). Reduction in pup body weight at 100 mg/kg/day (115-times the recommended dose based on AUC), which continued into the post-weaning maturation period, was associated with a slight decrease in pre-weaning survival and was considered adverse. No adverse effects were found in clinical observations, neurobehavioral assessment, or reproductive performance testing in the offspring of females treated with seladelpar. At 20 mg/kg/day (16-times the recommended dose based on AUC), none of the observed effects in offspring were considered to be adverse.

8.2 Lactation

Risk Summary

There are no data on the presence of seladelpar or its metabolite in either human or animal milk, the effects on the breastfed infant, or the effects on milk production. The developmental and health benefits of breastfeeding should be considered along with the mother's clinical need for LIVDELZI and any potential adverse effects on the breastfed infant from LIVDELZI or from the underlying maternal condition.

8.4 Pediatric Use

The safety and effectiveness of LIVDELZI in pediatric patients have not been established.

8.5 Geriatric Use

Of the 128 LIVDELZI-treated patients in Trial 1, 29 (23%) patients were 65 years of age and older and 2 (2%) were 75 years of age and older. No overall differences in safety or effectiveness were observed between patients 65 to 75 years of age and younger adult patients. No dosage adjustment for patients 65 years of age and older is necessary.

Clinical studies of LIVDELZI did not include sufficient numbers of patients 75 years of age and older to determine whether they respond differently from younger adult patients. Because of limited clinical experience with LIVDELZI in patients older than 75 years old, closer monitoring of adverse events in patients older than 75 years is recommended [see Clinical Pharmacology (12.3)].

8.6 Renal Impairment

The recommended dosage in patients with mild, moderate, or severe renal impairment is the same as in patients with normal renal function. Patients with end-stage renal disease on dialysis have not been studied [see Clinical Pharmacology (12.3)].

8.7 Hepatic Impairment

No dosage adjustment is recommended for PBC patients with mild hepatic impairment (Child-Pugh A) [see Clinical Pharmacology (12.3)].

The safety and efficacy of LIVDELZI in patients with decompensated cirrhosis have not been established. Use of LIVDELZI is not recommended in patients who have or develop decompensated cirrhosis (e.g., ascites, variceal bleeding, hepatic encephalopathy).

Monitor patients with cirrhosis for evidence of decompensation. Consider discontinuing LIVDELZI if the patient progresses to moderate or severe hepatic impairment (Child-Pugh B or C).

8.8 CYP2C9 Poor Metabolizers

Monitor CYP2C9 poor metabolizers who receive a concomitant moderate to strong CYP3A4 inhibitor more frequently for adverse reactions.

Seladelpar is a CYP2C9 and CYP3A4 substrate. Increased seladelpar AUC is expected in patients who are CYP2C9 poor metabolizers with concomitant use of a moderate to strong CYP3A4 inhibitor [see Drug Interactions (7.1), Clinical Pharmacology (12.5)].

10 OVERDOSAGE

PBC patients who received 5-times the recommended dosage or 20-times the recommended dosage of LIVDELZI experienced an increase in liver transaminases, muscle pain, and/or elevations in creatine phosphokinase, which resolved upon LIVDELZI discontinuation [see Warnings and Precautions (5.2)].

There is no specific treatment for overdose with LIVDELZI. General supportive care of the patient is indicated, as appropriate. If indicated, elimination of unabsorbed drug should be achieved by emesis or gastric lavage; usual precautions should be observed to maintain the airway. Because seladelpar is highly bound to plasma proteins, hemodialysis should not be considered.

11 DESCRIPTION

LIVDELZI capsules contain seladelpar lysine, a peroxisome proliferator-activated receptor (PPAR)-delta (δ) agonist. Seladelpar is a single enantiomer of the R-configuration and is present as a lysine dihydrate salt. Seladelpar lysine dihydrate is a white to off-white powder with a molecular formula of C21H23F3O5S ∙C6H14N2O2 ∙2H2O and a molecular weight of 626.7 g/mol. Its solubility in water is pH dependent. It is slightly soluble at low pH and very soluble at high pH. The chemical name for seladelpar lysine dihydrate is 2-[4-[[(2R)-2-ethoxy-3-[4-(trifluoromethyl)phenoxy]propyl]thio]-2-methylphenoxy]acetic acid, lysine dihydrate, and the chemical structure is:

LIVDELZI (seladelpar) capsules are supplied in a 10 mg strength for oral administration. Each capsule contains 14.1 mg of seladelpar lysine and the following inactive ingredients: butylated hydroxytoluene, colloidal silicon dioxide, croscarmellose sodium, magnesium stearate, mannitol, microcrystalline cellulose, and hard gelatin shells.

The light gray opaque (body)/dark blue opaque (cap) capsule shells contain gelatin, titanium dioxide, black iron oxide, yellow iron oxide, red iron oxide and the colorant FD&C Blue #2.

12 CLINICAL PHARMACOLOGY

12.1 Mechanism of Action

Seladelpar is a peroxisome proliferator-activated receptor (PPAR)-delta (δ) agonist. However, the mechanism by which seladelpar exerts its therapeutic effects in patients with PBC is not well understood. Pharmacological activity that is potentially relevant to therapeutic effects includes inhibition of bile acid synthesis through activation of PPARδ, which is a nuclear receptor expressed in most tissues, including the liver. Published studies show that PPARδ activation by seladelpar reduces bile acid synthesis through Fibroblast Growth Factor 21 (FGF21)-dependent downregulation of CYP7A1, the key enzyme for the synthesis of bile acids from cholesterol.

12.2 Pharmacodynamics

Pharmacodynamic Markers

In patients with PBC treated with 10 mg once daily of LIVDELZI (Trial 1), a greater reduction in mean ALP from baseline was observed as early as 1 month after treatment compared to the placebo group and lower ALP was generally maintained through month 12 [see Clinical Studies (14)].

In another study in which patients with PBC were treated with 2, 5, or 10 mg once daily of seladelpar, a dose dependent reduction in mean ALP was observed.

Cardiac Electrophysiology

At 20-times the recommended dose of 10 mg, LIVDELZI did not cause clinically significant QTc interval prolongation.

12.3 Pharmacokinetics

Following a single dose administration, seladelpar systemic exposure increased dose-proportionally from 2 mg (0.2 times the recommended dosage) to 15 mg (1.5 times the recommended dosage) and greater than dose proportionally at higher doses. For a dose increase from 10 mg to 200 mg (20 times the recommended dosage), mean Cmax and mean AUC for seladelpar increased 70-fold and 27-fold, respectively.

Following once daily dosing, seladelpar steady-state was achieved by day 4 and AUC increase was less than 30%. In PBC patients, median (CV) Cmax and AUC for seladelpar was 90.5 (42.5%) ng/mL and 817 (44%) ng*h/mL, respectively at steady state following once daily dosing of 10 mg.

Absorption

The median time to peak concentration (Tmax) was 1.5 hours for seladelpar.

Effect of Food

No clinically significant differences in seladelpar pharmacokinetics were observed following administration of a high-fat meal in healthy subjects.

Distribution

Seladelpar steady state apparent volume of distribution was approximately 110.3 L. Seladelpar plasma protein binding is greater than 99%.

Elimination

The apparent oral clearance of seladelpar is 12.6 L/h. Following administration of a single dose of 10 mg seladelpar in healthy subjects, mean elimination half-life was 6 hours for seladelpar. In PBC patients, the half-life range was 3.8 to 6.7 hours for seladelpar.

Metabolism

Seladelpar is primarily metabolized in vitro by CYP2C9 and to a lesser extent by CYP2C8 and CYP3A4, resulting in the three major metabolites: seladelpar sulfoxide (M1), desethyl-seladelpar (M2), and desethyl-seladelpar sulfoxide (M3). The metabolite-to-parent AUC ratios were 0.36, 2.32 and 0.63 for M1, M2 and M3, respectively. Median Tmax for metabolites were 10 hours for M1 and 4 hours for M2 and M3. None of the major metabolites have pharmacological activity.

Excretion

Seladelpar is primarily eliminated in urine as metabolites. Following a single oral dose of 10 mg radiolabeled seladelpar in humans, approximately 73.4% of the dose was recovered in urine (less than 0.01% unchanged) and 19.5% in feces (2.02% unchanged) within 216 hours. Biliary excretion of seladelpar was suggested by an animal study.

Specific Populations

No clinically significant differences in the pharmacokinetics of seladelpar were observed based on age (19 to 79 years old), body mass index (BMI) (17.6 to 45.0 kg/m^2), weight (45.8 to 127.5 kg), sex, and race (White, Black, or other).

Patients with Renal Impairment

In subjects with mild (eGFR ≥60 to <90 mL/min/1.73 m^2, MDRD), moderate (eGFR ≥30 to <60 mL/min/1.73 m^2), and severe (<30 mL/min/1.73 m^2 and not on dialysis) renal impairment, the AUCinf of seladelpar was 10% higher, 54% higher, and similar to that in subjects with normal renal function, respectively, after administration of a single 10 mg dose of seladelpar. The difference in Cmax of seladelpar was less than 18% in subjects with renal impairment compared to subjects with normal renal function [see Use in Specific Populations (8.6)]. The pharmacokinetics of seladelpar have not been studied in patients requiring hemodialysis.

Patients with Hepatic Impairment

Hepatic Impairment of various etiologies: Following a single oral dose of 10 mg seladelpar, seladelpar AUC increased 1.1-fold in subjects with mild (Child-Pugh A), 2.5-fold in moderate (Child-Pugh B), and 2.1-fold in severe (Child-Pugh C) hepatic impairment. Seladelpar Cmax increased 1.3-fold in subjects with mild (Child-Pugh A), 5.2-fold in moderate (Child-Pugh B), and 5-fold in severe (Child-Pugh C) hepatic impairment.

Hepatic Impairment in patients with PBC: Compared to PBC patients with mild hepatic impairment (Child-Pugh A) without portal hypertension, seladelpar exposures (Cmax, AUC) were 1.7 to 1.8-fold higher in PBC patients with mild hepatic impairment with portal hypertension, 1.6 to 1.9-fold higher in PBC patients with moderate hepatic impairment (Child-Pugh B), and 2.1 to 2.5-fold higher in PBC patients with severe hepatic impairment (Child-Pugh C) after a single oral dose of 10 mg seladelpar.

Accumulation ratios were less than 1.2-fold in PBC patients with mild hepatic impairment with portal hypertension and PBC patients with moderate hepatic impairment following 10 mg seladelpar once daily dosing for 28 days.

Drug Interaction Studies

Effect of Other Drugs on Seladelpar

Carbamazepine

Seladelpar AUC0–inf decreased by approximately 44% and Cmax by 24% following administration of a single 10 mg seladelpar dose after carbamazepine 300 mg twice daily for 8 days in healthy subjects. The carbamazepine (CYP3A and CYP2C9 inducer) dose was escalated from 100 mg twice daily for 3 days followed by 200 mg twice daily for 4 days to 300 mg twice daily.

Fluconazole

Seladelpar AUC0–inf increased by 2.4-fold and Cmax by 1.4-fold following concomitant use of a single 10 mg seladelpar dose with 400 mg fluconazole (moderate CYP2C9 and CYP3A4 inhibitor) in healthy subjects.

Cyclosporine

Seladelpar AUC0–inf increased by 2.1-fold and Cmax by 2.9-fold following concomitant use of a single 10 mg seladelpar dose with 600 mg cyclosporine (OATP1B1, OATP1B3, and BCRP inhibitor) in healthy subjects.

Probenecid

Seladelpar AUC0–inf increased by 2-fold and Cmax by 4.69-fold following concomitant use of a single 10 mg seladelpar dose with 500 mg probenecid in healthy subjects.

Quinidine

Seladelpar exposures were not significantly altered when a single dose of 600 mg quinidine (P-gp inhibitor) was coadministered in healthy subjects.

Other Drugs: No clinically significant differences in seladelpar pharmacokinetics were predicted when used concomitantly with strong CYP3A4 inhibitors or CYP2C8 inhibitors.

In Vitro Studies

Seladelpar is a substrate of CYP2C9, CYP2C8, CYP3A4, and the transporters BCRP, P-gp, OATP1B1, OATP1B3, and OAT3.

Seladelpar is not a substrate of MATE1, MATE2-K, OAT1, OCT1, or OCT2 transporters.

Effects of Seladelpar on other drugs

In clinical studies, no clinically significant differences in the pharmacokinetics of the following drugs were observed when used concomitantly with seladelpar: tolbutamide (CYP2C9 substrate), midazolam (CYP3A4 substrate), simvastatin (CYP3A4 and OATP substrate), atorvastatin (CYP3A4 and OATP substrate), or rosuvastatin (BCRP and OATP substrate).

In Vitro Studies

Based on in vitro studies, 10 mg seladelpar does not significantly affect the pharmacokinetics of concomitant drugs that are substrates of CYP enzymes (1A2, 2B6, 2C8, 2C19, 2D6, 3A4), UGTs, P-gp, MATEs, OCT1, OCT2, OAT1, or OAT3.

12.5 Pharmacogenomics

CYP2C9 activity is decreased in individuals with genetic variants such as CYP2C9*2 and CYP2C9*3. Compared to CYP2C9 normal metabolizers (*1/*1, n=84) after a single dose of seladelpar 1 mg to 15 mg, dose-normalized AUC0–inf was 48% higher in CYP2C9 poor metabolizers (*2/*3, n=2) and 24% higher in CYP2C9 intermediate metabolizers (*1/*2, *1/*8, *1/*3, *2/*2, n=28). Dose-normalized Cmax was similar for CYP2C9 normal, intermediate, and poor metabolizers. Seladelpar pharmacokinetics was not evaluated in patients who are CYP2C9 poor metabolizers with two no function alleles (e.g., *3/*3). CYP2C9 poor metabolizers may have increased AUC when seladelpar is used concomitantly with a moderate to strong CYP3A4 inhibitor [see Drug Interactions (7.1), Use in Specific Populations (8.8)].

The prevalence of CYP2C9 poor metabolizers is approximately 2 to 3% in White populations, 0.5 to 4% in Asian populations, and <1% in African American populations. Additional decreased or nonfunctional alleles (e.g., *5, *6, *11) are more prevalent in African American populations.

13 NONCLINICAL TOXICOLOGY

13.1 Carcinogenesis, Mutagenesis, Impairment of Fertility

Carcinogenesis

In a 2-year study in CD-1 mice, oral administration of seladelpar produced hepatocellular adenoma or carcinoma at a dose of 5 mg/kg/day in males (6-times the recommended dose based on AUC) and 20 mg/kg/day in females (140-times the recommended dose based on AUC). No tumorigenic effects were observed in female mice at doses of up to 10 mg/kg/day (49-times the recommended dose based on AUC).

In a 2-year study in Sprague-Dawley rats, oral administration of seladelpar produced benign interstitial cell tumors in testes and squamous cell carcinoma of the nonglandular stomach in males at a dose of 30 mg/kg/day (79-times the recommended dose based on AUC). No tumorigenic effects were observed in males at doses of up to 10 mg/kg/day (14-times the recommended dose based on AUC) or in females at doses of up to 30 mg/kg/day (26-times the recommended dose based on AUC).

Mutagenesis

Seladelpar was negative in the in vitro bacterial reverse mutation (Ames) assay, the in vitro mouse lymphoma assay, and the in vivo mouse micronucleus test.

Impairment of Fertility

Seladelpar had no effects on fertility or reproductive function in male and female rats at oral doses of up to 100 mg/kg/day (271-times and 115-times the maximum recommended dose in male and female rats, respectively, based on AUC).

13.2 Animal Toxicology and/or Pharmacology

In a 2-year study in CD-1 mice, seladelpar produced an increased incidence of lens cataracts at 5 mg/kg/day in both sexes (6-times and 19-times the recommended dose in male and female mice, respectively, based on AUC). In a 2-year study in Sprague-Dawley rats, seladelpar produced an increased incidence of cornea inflammation at 10 mg/kg/day (14-times the recommended dose based on AUC) and cornea mineralization at 30 mg/kg/day (79-times the recommended dose based on AUC), with both effects observed in males only. The incidence of cornea inflammation was not increased in male rats at 3 mg/kg/day (5-times the recommended dose based on AUC).

14 CLINICAL STUDIES

The efficacy of LIVDELZI was evaluated in Trial 1 (NCT04620733), a 12-month, randomized, double-blind, placebo-controlled trial. The trial included 193 adult patients with PBC with an inadequate response or intolerance to UDCA. Patients were included in the trial if their ALP was greater than or equal to 1.67-times the ULN and total bilirubin (TB) was less than or equal to 2-times the ULN. Patients were excluded from the trial if they had other chronic liver diseases, clinically important hepatic decompensation including portal hypertension with complications, or cirrhosis with complications (e.g., Model for End Stage Liver Disease [MELD] score of 12 or greater, known esophageal varices or history of variceal bleeds, history of hepatorenal syndrome).

Patients were randomized to receive LIVDELZI 10 mg (N=128) or placebo (N=65) once daily for 12 months. LIVDELZI or placebo was administered in combination with UDCA in 181 (94%) patients during the trial, or as a monotherapy in 12 (6%) patients who were unable to tolerate UDCA.

Baseline Demographics and Characteristics

The mean age of patients was 57 (Range: 28 to 75) years; 95% were female; 88% were White, 6% Asian, 2% Black or African American, and 3% American Indian or Alaska Native. Twenty-nine percent of the patients, 23% in the LIVDELZI 10 mg arm and 42% in the placebo arm, identified as Hispanic/Latino. Thirty-two percent of the patients, 38% in the LIVDELZI 10 mg arm and 20% in the placebo arm, were enrolled in the US.

At baseline, 18 (14%) of the LIVDELZI-treated patients and 9 (14%) of the placebo-treated patients met at least one of the following criteria: Fibroscan >16.9kPa; historical biopsy or radiological evidence suggestive of cirrhosis; platelet count <140,000/µL with at least one additional laboratory finding including serum albumin <3.5 g/dL, INR >1.3, or TB > 1-time ULN; or clinical determination of cirrhosis by the investigator.

The mean baseline ALP concentration was 314 (Range: 161 to 786) units per liter (U/L), corresponding to 2.7-times ULN. The mean baseline TB concentration was 0.8 (Range: 0.3 to 1.9) mg/dL and was less than or equal to the ULN in 87% of the patients. Other mean baseline liver biochemistries were 48 (Range: 9 to 115) U/L for ALT and 40 (Range: 16 to 94) U/L for AST.

Biochemical Results

The primary endpoint was biochemical response at Month 12, where biochemical response was defined as achieving ALP less than 1.67-times ULN, an ALP decrease of greater than or equal to 15% from baseline, and TB less than or equal to ULN. ALP normalization (i.e., ALP less than or equal to ULN) at Month 12 was a key secondary endpoint. The ULN for ALP was defined as 116 U/L. The ULN for TB was defined as 1.1 mg/dL.

Table 3 presents results at Month 12 for the percentage of patients who achieved biochemical response, achieved each component of biochemical response, and achieved ALP normalization. LIVDELZI demonstrated greater improvement on biochemical response and ALP normalization at Month 12 compared to placebo. Overall, 87% of patients had a baseline of TB concentration less than or equal to ULN. Therefore, improvement in ALP was the main contributor to the biochemical response rate results at Month 12.

Table 3: Percentage of Adult Patients with PBC Achieving Biochemical Response and ALP Normalization at Month 12 in Trial 1 [Biochemical response is defined as ALP less than 1.67-times ULN, an ALP decrease of greater than or equal to 15%, and TB less than or equal to ULN.]
 | LIVDELZI 10 mg Once Daily (N=128) | Placebo (N=65) | Treatment Difference % (95% CI) [95% unstratified Miettinen and Nurminen confidence intervals (CIs) are provided.]
Biochemical Response Rate, n (%), [p<0.0001 for LIVDELZI 10 mg versus placebo. P-values were obtained using the Cochran–Mantel–Haenszel test stratified by baseline ALP level (<350 U/L versus ≥350 U/L) and baseline pruritus NRS (<4 versus ≥4).] | 79 (62) | 13 (20) | 42 (28, 53)
Components of Biochemical Response
ALP less than 1.67-times ULN, n (%) | 84 (66) | 17 (26) | 39 (25, 52)
Decrease in ALP of at least 15%, n (%) | 107 (84) | 21 (32) | 51 (37, 63)
TB less than or equal to ULN, n (%) | 104 (81) | 50 (77) | 4 (-7, 17)
ALP Normalization, n (%), [ALP normalization is defined as ALP less than or equal to ULN.] | 32 (25) | 0 (0) | 25 (18, 33)
Patients who discontinued treatment prior to Month 12 or who had missing data were considered as non-responders.

Figure 1 shows the mean (95% CI) levels of ALP over 12 months. There was a trend of lower ALP in LIVDELZI arm compared to placebo arm starting at Month 1 through Month 12.

Figure 1: Mean [Figure 1 presents means and 95% Wald CIs for baseline, and least squares means and corresponding 95% CIs based on a mixed-effect model for repeated measures (MMRM) for Months 1, 3, 6, 9 and 12. The MMRM adjusts for baseline ALP, baseline ALP level (<350 U/L versus ≥350 U/L), baseline pruritus NRS (<4 versus ≥4), time (in months), treatment arm, treatment-by-baseline ALP interaction, and treatment-by-time interaction. The least squares mean change from baseline in ALP at Month 12 was -134 (-151, -117) U/L and -17 (-40, 6) U/L in the LIVDELZI 10 mg and placebo arms, respectively.] ALP in Adult Patients with PBC over 12 Months in Trial 1

Biochemical response at Month 3 comparing LIVDELZI as a monotherapy to placebo was evaluated in a pooled analysis of a subset of patients from Trial 1 and another randomized, double-blind, placebo-controlled trial in a similar patient population. There was a trend of improvement on biochemical response at Month 3 in the LIVDELZI monotherapy group compared to the placebo group.

Pruritus

A single-item patient-reported outcome (PRO), the pruritus Numerical Rating Scale (NRS), evaluated patients' daily worst itching intensity on an 11-point rating scale with scores ranging from 0 ("no itching") to 10 ("worst itching imaginable") in Trial 1. The pruritus NRS was administered daily in a 14-day run-in period prior to randomization through Month 6.

Table 4 presents the results of the comparison between LIVDELZI and placebo on the key secondary endpoint evaluating the change from baseline in pruritus score at Month 6 in patients with baseline average pruritus scores greater than or equal to 4. The baseline average pruritus score for each patient was calculated by averaging the pruritus NRS scores administered in the run-in period and on Day 1 before treatment initiation. The pruritus scores at Month 6 for each patient were calculated by averaging the pruritus NRS scores within the last week in the month. Patients treated with LIVDELZI demonstrated greater improvement in pruritus compared with placebo.

Table 4: Change from Baseline in Pruritus Score at Month 6 in PBC Patients with Baseline Average Pruritus Score ≥4 in Trial 1 [Based on least square means from a mixed-effect model for repeated measures (MMRM) for change from baseline at Months 1 (Week 4), 3 (Week 12), and 6 (Week 26) accounting for baseline average pruritus score, baseline ALP level (<350 U/L versus ALP level ≥350 U/L), treatment arm, time (in months), and treatment-by-time interaction.]
 | LIVDELZI 10 mg Once Daily (N=49) | Placebo (N=23)
Baseline Average Pruritus Score, Mean (SD) | 6.1 (1.4) | 6.6 (1.4)
Change from Baseline in Pruritus Score at Month 6
Mean (SE) | -3.2 (0.3) | -1.7 (0.4)
Mean difference vs. placebo (95% CI) | -1.5 (-2.5, -0.5) p=0.0051

16 HOW SUPPLIED/STORAGE AND HANDLING

How Supplied

LIVDELZI (seladelpar) capsules are available as 10 mg, light gray opaque body, and a dark blue opaque cap with "CBAY" imprinted on the cap and "10" on the body.

LIVDELZI is packaged in a high density polyethylene bottle, closed with a polypropylene child resistant cap containing an induction seal.

- 10 mg capsules in a 75 cc bottle (30 count) (NDC 61958-3301-1).
- 10 mg capsules in a 60 cc bottle (30 count) (NDC 61958-3301-2).

Storage and Handling

Store at 20°C to 25°C (68°F to 77°F); excursions permitted to 15°C to 30°C (59°F to 86°F) [see USP Controlled Room Temperature].

Dispense only in original container to protect from light.

17 PATIENT COUNSELING INFORMATION

Advise the patient to read the FDA-approved patient labeling (Patient Information).

Fractures

Inform patients that LIVDELZI may increase the risk of bone fractures. Advise patients to call their healthcare provider to report any fractures [see Warnings and Precautions (5.1)].

Liver Test Abnormalities

Instruct patients to report any signs or symptoms of liver-related adverse reactions (e.g., loss of appetite, nausea, increased fatigue, lower extremity edema, abdominal swelling, or jaundice/icterus) to their healthcare provider [see Warnings and Precautions (5.2)].

Biliary Obstruction

Instruct patients to immediately report any signs or symptoms of biliary obstruction (e.g., right upper quadrant pain, jaundice) to their healthcare provider so that LIVDELZI treatment can be interrupted while the patient is being evaluated [see Warnings and Precautions (5.3)].

Pregnancy

Advise patients that there is a pregnancy safety study that captures pregnancy outcomes in women exposed to LIVDELZI during pregnancy, and to report pregnancies and pregnancy outcomes by calling 1-800-445-3235 [see Use in Specific Populations (8.1)].

Distributed by: Gilead Sciences, Inc., Foster City, CA 94404.

LIVDELZI is a trademark of Gilead Sciences, Inc., or its related companies.

Copyright © 2026 Gilead Sciences, Inc. All rights reserved.

PATIENT INFORMATION
LIVDELZI (liv del' zee)
(seladelpar)
capsules, for oral use

What is LIVDELZI?

LIVDELZI is a prescription medicine used to treat primary biliary cholangitis (PBC) in combination with ursodeoxycholic acid (UDCA) in adults who have not responded well to UDCA or used alone in patients unable to tolerate UDCA.

LIVDELZI is not recommended for use in people who have advanced liver disease (decompensated cirrhosis). Symptoms of advanced liver disease may include confusion, having fluid in the stomach-area (abdomen), black, tarry, or bloody stools, coughing up or vomiting blood, or having vomit that looks like "coffee grounds".

It is not known if taking LIVDELZI will improve your chance of survival or prevent liver decompensation.

It is not known if LIVDELZI is safe and effective in children.

Before taking LIVDELZI, tell your healthcare provider about all your medical conditions, including if you:

- have advanced liver disease.
- think you may have a blockage of the bile ducts in your liver (biliary obstruction).
- are pregnant or plan to become pregnant. It is not known if LIVDELZI will harm your unborn baby.
  - Pregnancy safety study. If you become pregnant while taking LIVDELZI, tell your healthcare provider right away. There is a pregnancy safety study for women who take LIVDELZI during pregnancy. Talk to your healthcare provider about providing information to the LIVDELZI pregnancy safety study. The purpose of this pregnancy safety study is to capture information about your health and your baby's health. You or your healthcare provider can report your pregnancy by calling 1-800-445-3235.
- are breastfeeding or plan to breastfeed. It is not known if LIVDELZI passes into your breast milk. Talk with your healthcare provider about the best way to feed your baby if you take LIVDELZI.

Tell your healthcare provider about all the medicines you take, including prescription and over-the-counter medicines, vitamins, and herbal supplements. Certain other medicines may affect the way LIVDELZI works.

How should I take LIVDELZI?

- Take LIVDELZI exactly as your healthcare provider tells you to.
- Do not take more LIVDELZI than your healthcare provider tells you to.
- Take LIVDELZI by mouth 1 time each day.
- Take LIVDELZI with or without food.
- If you also take medicines to help lower your cholesterol (bile acid binding resins), take LIVDELZI at least 4 hours before or 4 hours after you take the bile acid binding resin. If this is not possible, space the time between taking LIVDELZI and your bile acid binding resin as far apart as possible.
- If you take too much LIVDELZI, call your healthcare provider or get emergency medical help right away.

What are the possible side effects of LIVDELZI?

LIVDELZI can cause serious side effects, including:

- bone fractures. Taking LIVDELZI may increase your risk of bone fractures. Tell your healthcare provider about any bone fractures, or if you develop pain, or have changes in your ability to move around.
- changes in liver tests. Increased liver enzymes in the blood have happened when taking more LIVDELZI than prescribed. Your healthcare provider will do tests to check your liver before you start and during treatment with LIVDELZI.
  Tell your healthcare provider right away if you have any of the following signs or symptoms of worsening liver problems during treatment with LIVDELZI:

- swelling of your stomach-area (abdomen) from a build-up of fluid
- yellowing of your skin or the whites of your eyes
- pain on the right side of your stomach (abdomen)
- black, tarry, or bloody stools
- coughing up or vomiting blood, or your vomit looks like "coffee grounds"

- mental changes such as confusion, being sleepier than usual or harder to wake up, slurred speech, mood swings, or changes in personality

The most common side effects of LIVDELZI include:

- headache
- stomach (abdominal) pain
- nausea

- abdominal swelling (distension)
- dizziness

Tell your healthcare provider if you have any side effect that bothers you or does not go away.

These are not all the possible side effects of LIVDELZI. Call your doctor for medical advice about side effects. You may report side effects to FDA at 1-800-FDA-1088.

How should I store LIVDELZI?

- Store LIVDELZI at room temperature between 68°F to 77°F (20°C to 25°C)
- Store in the original container to protect LIVDELZI from light.

Keep LIVDELZI and all medicines out of the reach of children.

General information about the safe and effective use of LIVDELZI.

Medicines are sometimes prescribed for purposes other than those listed in a Patient Information leaflet. Do not use LIVDELZI for a condition for which it was not prescribed. Do not give LIVDELZI to other people, even if they have the same symptoms that you have. It may harm them. You can ask your pharmacist or healthcare provider for information about LIVDELZI that is written for health professionals.

What are the ingredients in LIVDELZI?

Active ingredient: seladelpar lysine

Inactive ingredients: butylated hydroxytoluene, colloidal silicon dioxide, croscarmellose sodium, magnesium stearate, mannitol, microcrystalline cellulose, and hard gelatin shells.

The light gray opaque (body) and dark blue opaque (cap) capsule shells contain gelatin, titanium dioxide, black iron oxide, yellow iron oxide, red iron oxide and the colorant FD&C Blue #2.

Distributed by: Gilead Sciences, Inc., Foster City, CA 94404.

LIVDELZI is a trademark of Gilead Sciences, Inc., or its related companies.

© 2026 Gilead Sciences, Inc. All rights reserved. 217899-GS-002

For more information, call 1-800-445-3235 or go to www.LIVDELZI.com.

This Patient Information has been approved by the U.S. Food and Drug Administration.

Revised: 01/2026

PRINCIPAL DISPLAY PANEL - 10 mg Capsule Bottle Label

NDC 61958-3301-1

Livdelzi®
seladelpar

10 mg

For Oral Use Only
30 capsules

Rx only
GILEAD

PRINCIPAL DISPLAY PANEL - 10 mg Capsule Bottle Label

NDC 61958-3301-2

Livdelzi®
seladelpar

10 mg

For Oral Use Only
30 capsules

Rx only
GILEAD